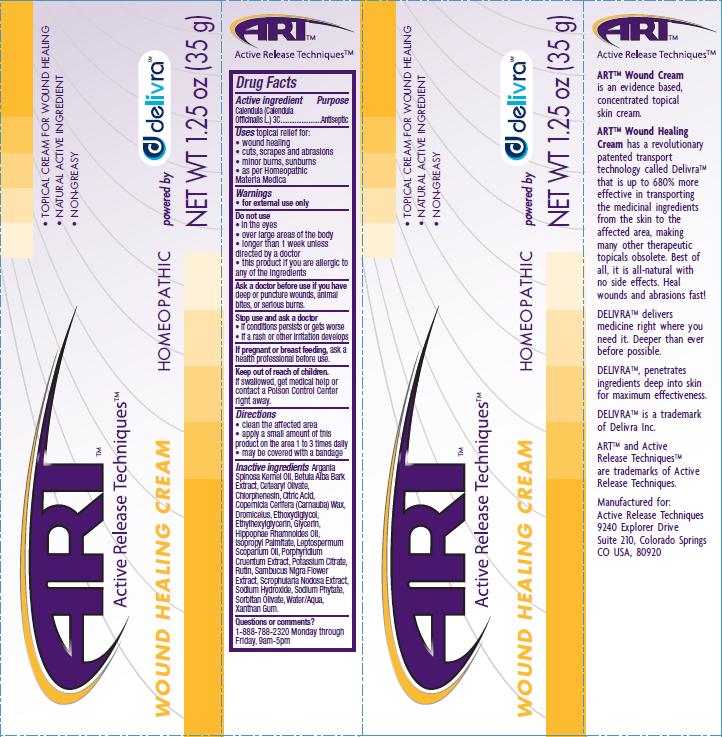 DRUG LABEL: Wound Healing 
NDC: 76029-003 | Form: CREAM
Manufacturer: Active Release Techniques
Category: homeopathic | Type: HUMAN OTC DRUG LABEL
Date: 20110330

ACTIVE INGREDIENTS: CALENDULA OFFICINALIS FLOWERING TOP 3 [hp_C]/35 g
INACTIVE INGREDIENTS: ARGAN OIL; BETULA PUBESCENS BARK; CETEARYL OLIVATE; CHLORPHENESIN; CITRIC ACID MONOHYDRATE; CARNAUBA WAX; DIETHYLENE GLYCOL MONOETHYL ETHER; GLYCERIN; ISOPROPYL PALMITATE; LEPTOSPERMUM PETERSONII LEAF OIL; PORPHYRIDIUM PURPUREUM; POTASSIUM CITRATE; RUTIN; SAMBUCUS NIGRA FLOWER; SCROPHULARIA NODOSA; SODIUM HYDROXIDE; SORBITAN OLIVATE; WATER; XANTHAN GUM

ACTIVE INGREDIENT

Calendula (Calendula Officinalis)

PURPOSE

Antiseptic

INDICATIONS AND USAGE

Topical relief for:

- wound healing
- cuts, scrapes and abrasions
- minor burns, sunburns

as per Homeopathic Materia Medica

WARNINGS

for external use only

Do not use:

- in the eyes
- over large areas of the body
- longer than 1 week unless directed by a doctor
- this product if you are allergic to any of the ingredients

Ask a doctor before use if you have deep or puncture wounds, animal bites or serious burns.

Stop use and ask a doctor:

- if condition persists or gets worse
- if a rash or other irritation develops

PREGNANCY OR BREAST FEEDING

If pregnant or breast feeding, ask a health professional before use.

Keep out of reach of children. If swallowed, get medical help or contact a Poison Control Center right away.

Directions:

- clean the affected area
- apply a small amount of this product on the area 1 to 3 times daily
- may be covered with a bandage

INACTIVE INGREDIENT

Argania Spinosa Kernel Oil, Betula Alba Bark Extract, Cetearyl Olivate, Chlorphenesin, Citric Acid, Copernicia Cerifera (Carnauba) Wax, Dromiceius, Ethoxydiglycol, Glycerin, Hippophae Rhamnoides Oil, Isopropyl Palmitate, Leptospermum Scoparium Oil, Porphyridium Cruentum Extract, Potassium Citrate, Rutin, Sambucus Nigra Flower Extract, Scrophularia Nodosa Extract, Sodium Hydroxide, Sodium Phytate, Sorbitan Olivate, Water/Aqua, Xanthan Gum

Questions or Comments?

1-888-788-2320 Monday through Friday, 9am-5pm

PACKAGE LABEL

- Topical Cream for Wound Healing
- Natural Active Ingredient
- Non-Greasy